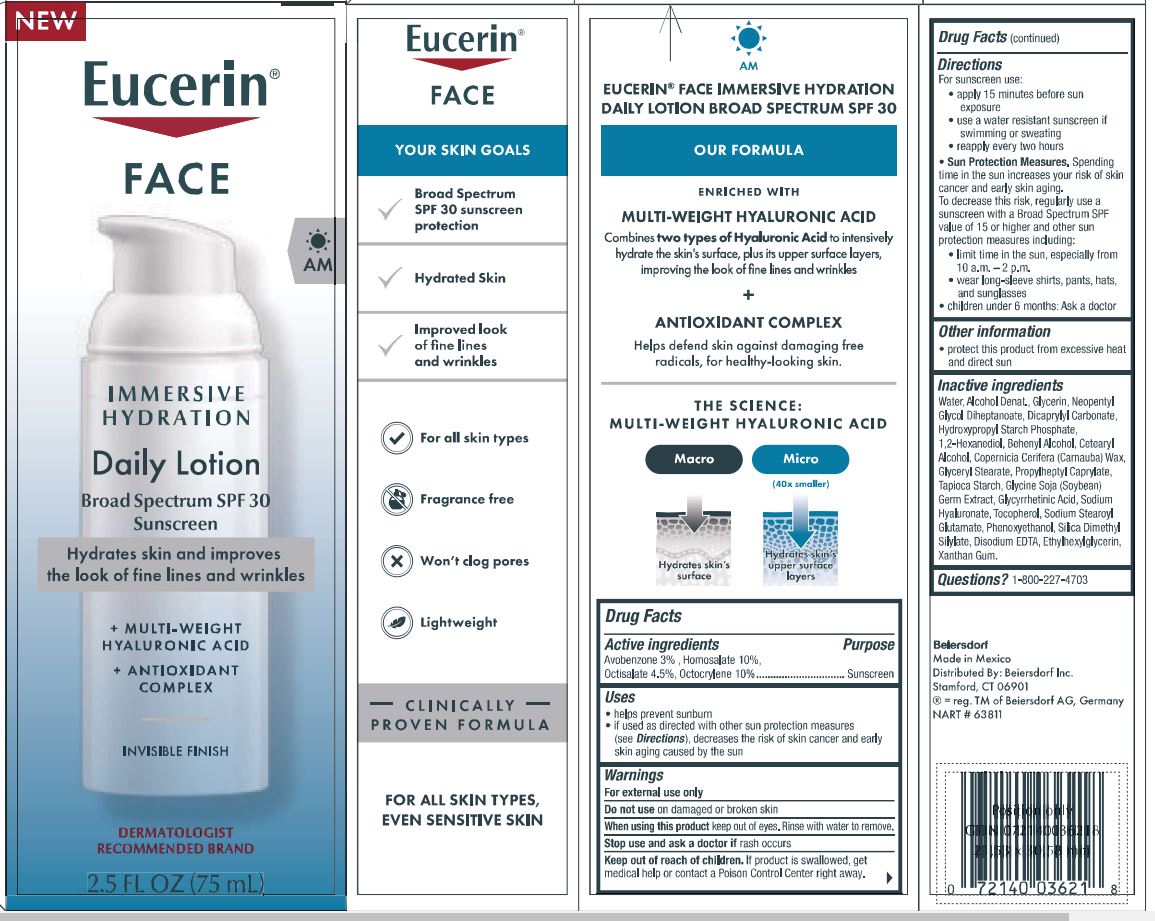 DRUG LABEL: Eucerin Face immersive Hydration
NDC: 10356-385 | Form: LOTION
Manufacturer: Beiersdorf Inc
Category: otc | Type: HUMAN OTC DRUG LABEL
Date: 20251231

ACTIVE INGREDIENTS: OCTOCRYLENE 10 g/100 g; HOMOSALATE 10 g/100 g; AVOBENZONE 3 g/100 g; OCTISALATE 4.5 g/100 g
INACTIVE INGREDIENTS: NEOPENTYL GLYCOL DIHEPTANOATE; PROPYLHEPTYL CAPRYLATE; SOYBEAN GERM; ALCOHOL; ETHYLHEXYLGLYCERIN; EDETATE DISODIUM; DICAPRYLYL CARBONATE; CARNAUBA WAX; HYALURONATE SODIUM; SODIUM STEAROYL GLUTAMATE; 1,2-HEXANEDIOL; GLYCERYL MONOSTEARATE; STARCH, TAPIOCA; ENOXOLONE; CETOSTEARYL ALCOHOL; TOCOPHEROL; WATER; GLYCERIN; SILICA DIMETHYL SILYLATE; PHENOXYETHANOL; XANTHAN GUM

Eucerin Face Immersive Hydration Daily Lotion

Active ingredients

Avobenzone 3%

Homosalate 10%

Octisalate 4.5%

Octocrylene 10%

Purpose

Sunscreens

Uses
• helps prevent sunburn
• if used as directed with other sun protection measures (see Directions),
decreases the risk of skin cancer and early skin aging caused by the sun

Warnings
For external use only

.

Do not use on damaged or broken skin.

When using this product keep out of eyes. Rinse with water to remove.

Stop use and ask a doctor if rash occurs

Keep out of reach of children. If swallowed, get medical help or contact a Poison Control Center right away.

Directions

For sunscreen use:
• apply liberally 15 minutes before sun exposure
• use a water resistant sunscreen if swimming or sweating
• reapply at least every 2 hours
• children under 6 months of age: Ask a doctor
• Sun Protection Measures. Spending time in the sun increases your risk of skin cancer and
early skin aging. To decrease this risk, regularly use a sunscreen with a Broad Spectrum SPF
value of 15 or higher, and other sun protection measures including:
• limit time in the sun, especially from 10 a.m. - 2 p.m.
• wear long-sleeved shirts, pants, hats, and sunglasses.
• children under 6 months of age: Ask a doctor.

Other information

protect this product from excessive heat and direct sun

Inactive ingredients

Water, Alcohol Denat., Glycerin, Neopentyl
Glycol Diheptanoate, Dicaprylyl Carbonate,
Hydroxypropyl Starch Phosphate,
1,2-Hexanediol, Behenyl Alcohol, Cetearyl
Alcohol, Copernicia Cerifera (Carnauba) Wax,
Glyceryl Stearate, Propylheptyl Caprylate,
Tapioca Starch, Glycine Soja (Soybean)
Germ Extract, Glycyrrhetinic Acid, Sodium
Hyaluronate, Tocopherol, Sodium Stearoyl
Glutamate, Phenoxyethanol, Silica Dimethyl
Silylate, Disodium EDTA, Ethylhexylglycerin,
Xanthan Gum.

PACKAGE LABEL

Eucerin

Face

Immersive Hydration

Daily Lotion

Broad Spectrum SPF 30
Sunscreen
Hydrates skin and improves the look of fine lines and wrinkles

+ MULTI-WEIGHT HYALURONIC ACID + ANTIOXIDANT COMPLEX

INVISIBLE FINISH
DERMATOLOGIST RECOMMENDED BRAND